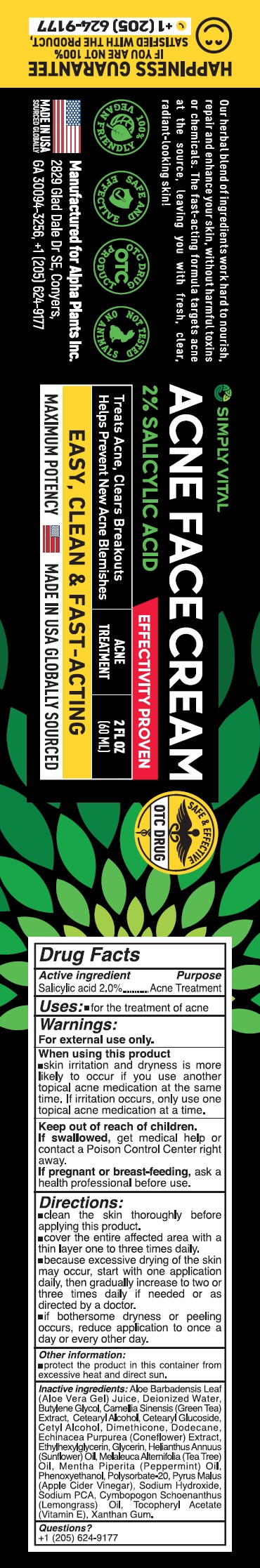 DRUG LABEL: SIMPLY VITAL Acne Face Cream
NDC: 82460-272 | Form: CREAM
Manufacturer: ALPHA PLANTS INC
Category: otc | Type: HUMAN OTC DRUG LABEL
Date: 20231111

ACTIVE INGREDIENTS: SALICYLIC ACID 20 mg/1 mL
INACTIVE INGREDIENTS: ALOE VERA LEAF; WATER; BUTYLENE GLYCOL; GREEN TEA LEAF; CETOSTEARYL ALCOHOL; CETEARYL GLUCOSIDE; CETYL ALCOHOL; DIMETHICONE; DODECANE; ECHINACEA PURPUREA WHOLE; ETHYLHEXYLGLYCERIN; GLYCERIN; HELIANTHUS ANNUUS FLOWERING TOP; TEA TREE OIL; PEPPERMINT OIL; PHENOXYETHANOL; POLYSORBATE 20; APPLE CIDER VINEGAR; SODIUM HYDROXIDE; SODIUM PYRROLIDONE CARBOXYLATE; CYMBOPOGON SCHOENANTHUS OIL; .ALPHA.-TOCOPHEROL ACETATE; XANTHAN GUM

SIMPLY VITAL Acne Face Cream

Active ingredient

Salicylic acid 2.0%

Purpose

Acne Treatment

Uses:

- for the treatment of acne

Warnings:

For external use only.

When using this product

skin irritation and dryness is more likely to occr if you use another topical acne medication at the same time. If irritation occurs, only use one topical acne medication at a time.

Keep out of reach of children.

If swallowed, get medical help or contact a Poison Control Center right away.

If pregnant or breast-feeding,

ask a health professional before use.

Directions:

- clean the skin thoroughly before applying this product.
- cover the entire affected area with a thin layer one to three times daily.
- because excessive drying of the skin may occur, start with one appilcation daily, then gradually increase to two or three times daily if needed or as directed by a doctor.
- if bothersome dryness or peeling occur, reduce application to once a day or every other day.

Other information:

- protect the product in this container from excessive heat and direct sun.

Inactive ingredients:

Aloe Barbadensis Leaf (Aloe Vera Gel) Juice, Deionized Water, Butylene Glycol, Camellia Sinensis (Green Tea) Extract, Cetearyl Alcohol, Cetearyl Glucoside, Cetyl Alcohol, Dimethicone, Dodecane, Echinacea Purpurea (Coneflower) Extract, Ethylhexylglycerin, Glycerin, Helianthus Annuus (Sunflower) Oil, Melaleuca Alternifolia (Tea Tree) Oil, Mentha Piperita (Peppermint) Oil, Phenoxyethanol, Polysorbate-20, Pyrus Malus (Apple Cider Vinegar), Sodium Hydroxide, Sodium PCA, Cymbopogon Schoenanthus (Lemongrass) Oil, Tocopheryl Acetate (Vitamin E), Xanthan Gum.

Questions?

+1 (205) 624-9177